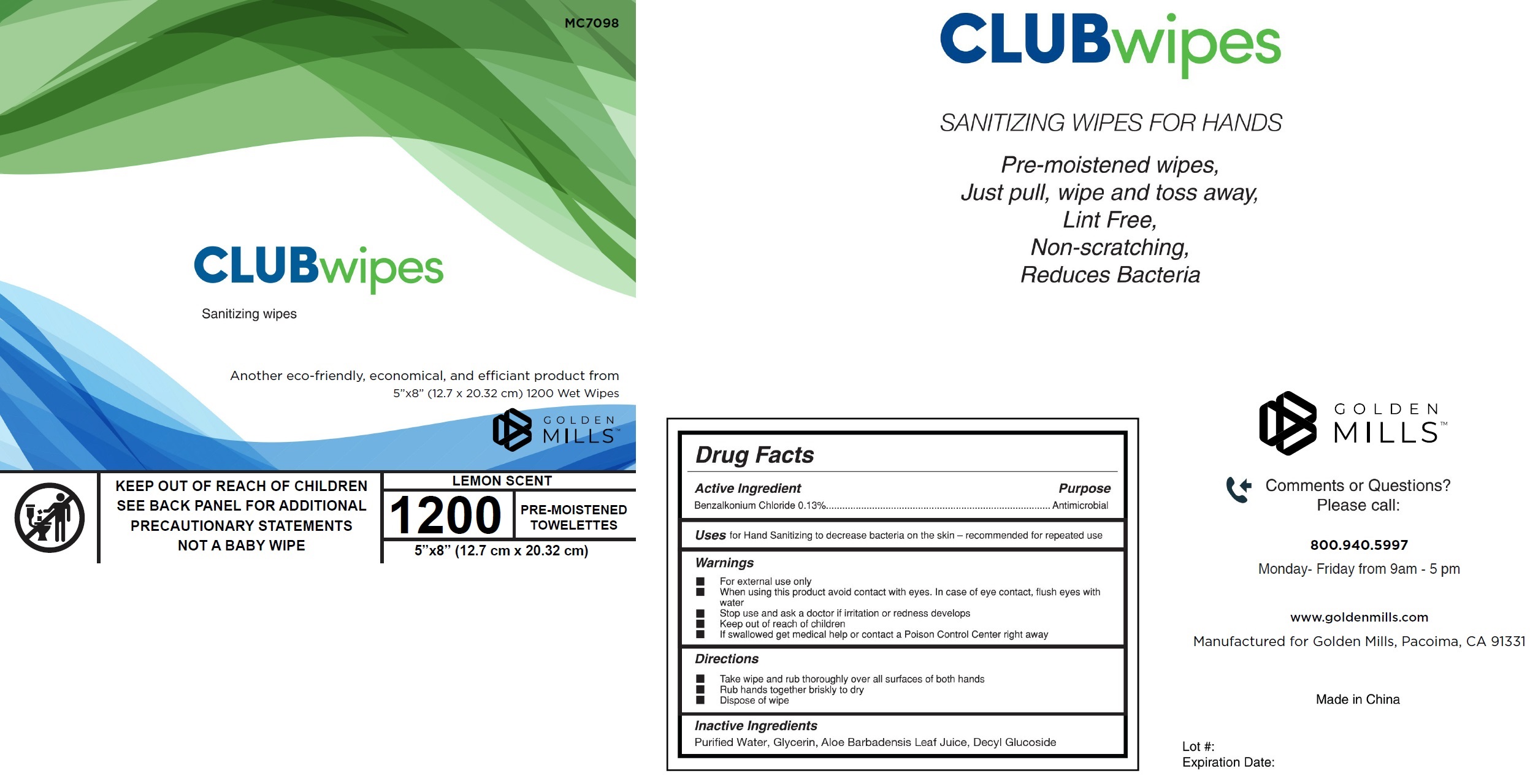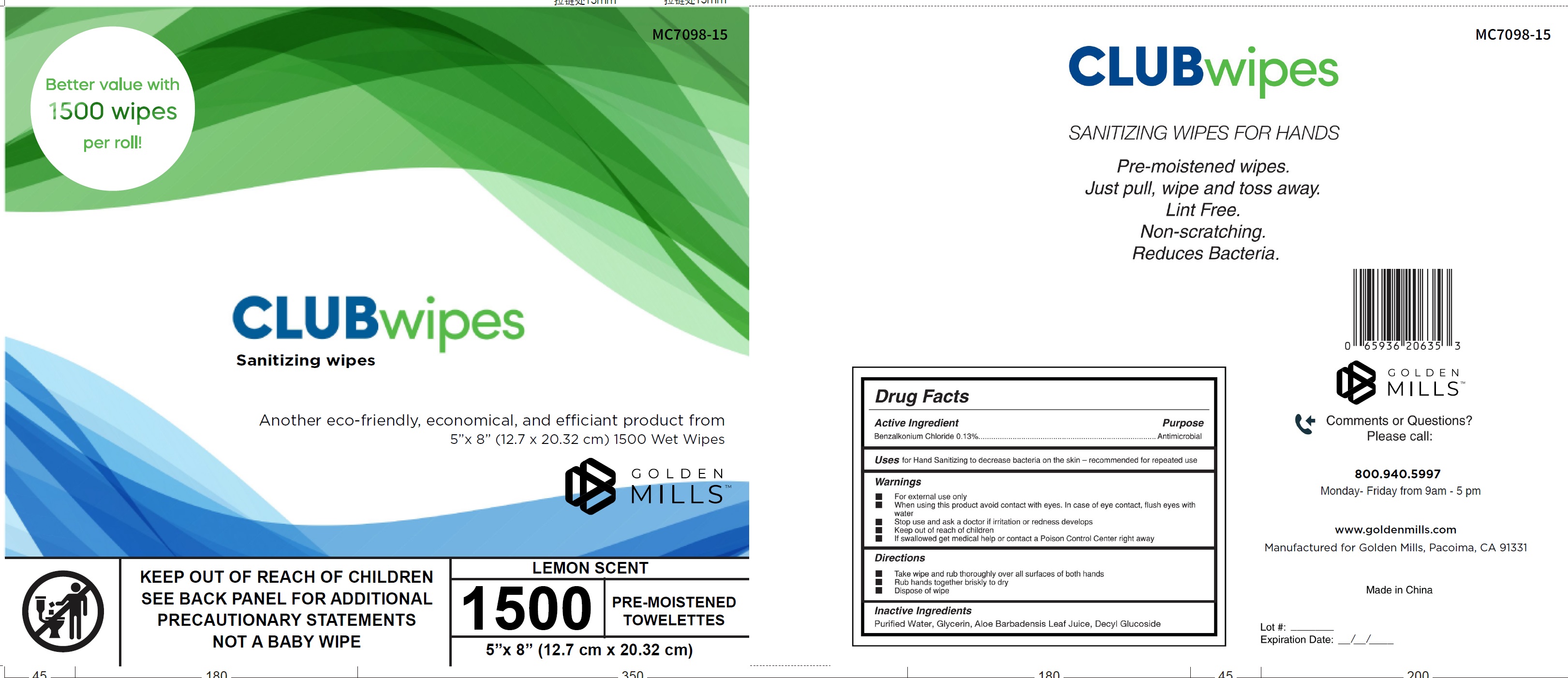 DRUG LABEL: Club Wipes Sanitizing Wipes Lemon Scent
NDC: 78940-010 | Form: CLOTH
Manufacturer: Golden Mills LLC
Category: otc | Type: HUMAN OTC DRUG LABEL
Date: 20251105

ACTIVE INGREDIENTS: BENZALKONIUM CHLORIDE 1.3 mg/1 g
INACTIVE INGREDIENTS: WATER; GLYCERIN; ALOE VERA LEAF; DECYL GLUCOSIDE

Club Wipes Sanitizing Wipes, Lemon Scent

Active Ingredient

Benzalkonium Chloride 0.13%

Purpose

Antimicrobial

Uses

for Hand Sanitizing to decrease on the skin - recommended for repeated use

Warnings

- For external use only

When using this product

- avoid contact with eyes. In case of eye contact, flush eyes with water

Stop use and ask a doctor

- if irritation or redness develops

Keep out of reach of children

- If swallowed get medical help or contact a Poison Control Center right away

Directions

- Take wipe and rub thoroughly over all surfaces or both hands
- Rub hands together briskly to dry
- Dispose of wipe

Inactive Ingredients

Purified Water, Glycerin, Aloe Barbadensis Leaf Juice, Decyl Glucoside